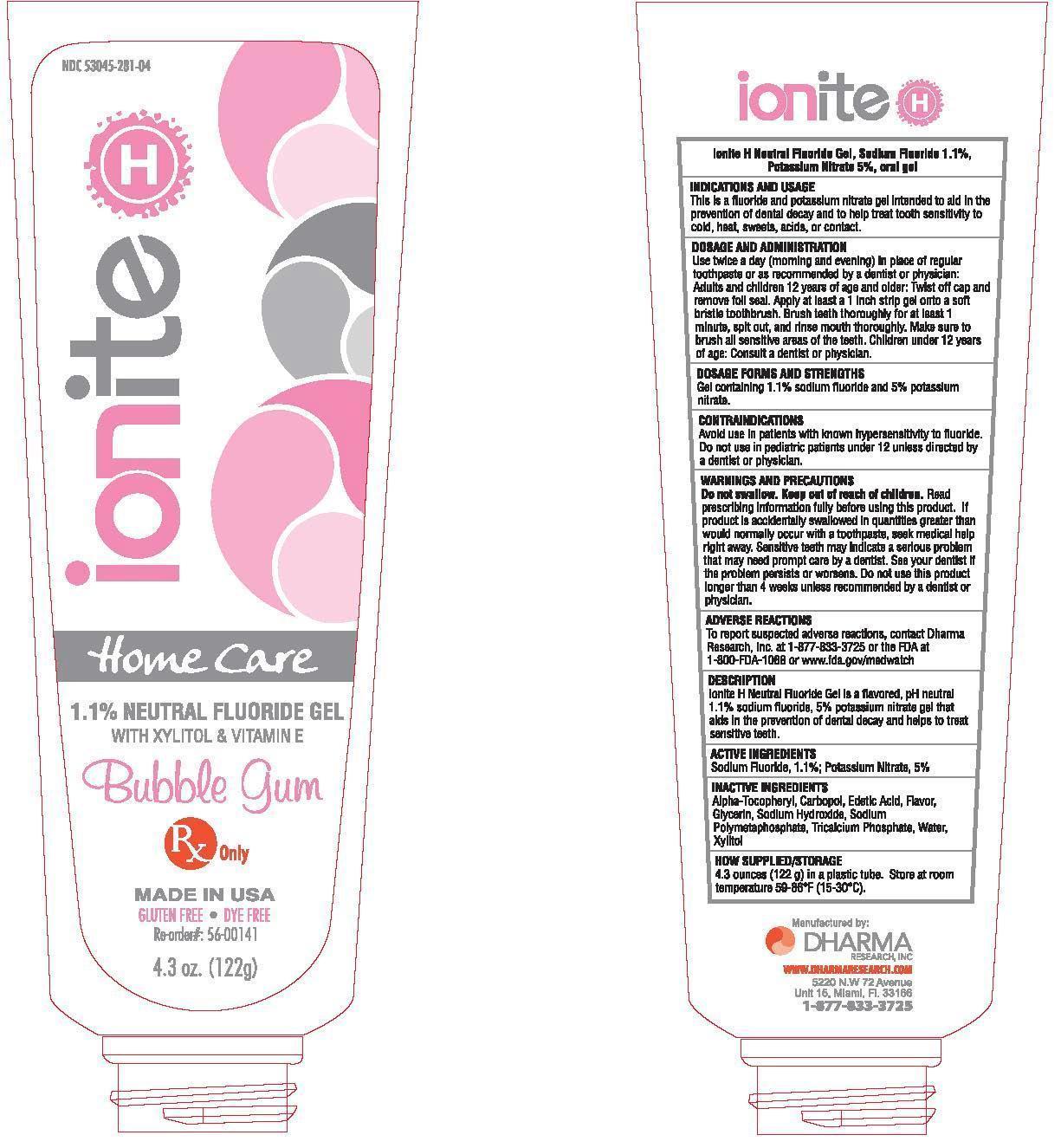 DRUG LABEL: Ionite H
NDC: 53045-281 | Form: GEL, DENTIFRICE
Manufacturer: Dharma Research, Inc.
Category: prescription | Type: HUMAN PRESCRIPTION DRUG LABEL
Date: 20150802

ACTIVE INGREDIENTS: SODIUM FLUORIDE 1.1 mg/100 g; POTASSIUM NITRATE 5 mg/100 g
INACTIVE INGREDIENTS: .ALPHA.-TOCOPHEROL; CARBOMER HOMOPOLYMER TYPE C (ALLYL PENTAERYTHRITOL CROSSLINKED); EDETIC ACID; GLYCERIN; SODIUM HYDROXIDE; SODIUM POLYMETAPHOSPHATE; TRICALCIUM PHOSPHATE; water; XYLITOL

Ionite H Neutral Fluoride Gel, Sodium Fluoride, 1.1%, Potassium Nitrate, 5%, oral gel

INDICATIONS AND USAGE

This is a fluoride and potassium nitrate gel intended to aid in the prevention of dental decay and to help treat tooth sensitivity to cold, heat, sweets, acids, or contact.

DOSAGE AND ADMINISTRATION

Use twice per day (morning and evening) in place of regular toothpaste or as recommended by a dentist or physician.

Adults and children 12 years of age and older: Twist off cap and remove foil seal. Apply at least a 1 inch strip gel onto a soft bristle tooth brush. Brush teeth thoroughly for at least 1 minute, spit out, and rinse mouth thoroughly. Make sure to brush all sensitive areas of the teeth.

Children under 12 years of age: consult a dentist or physician.

DOSAGE FORMS AND STRENGTHS

Gel containing 1.1% sodium fluoride and 5% potassium nitrate.

CONTRAINDICATIONS

Avoid use in patients with known hypersensitivity to fluoride. Do not use in pediatric patients under 12 unless directed by a dentist or physician.

WARNINGS AND PRECAUTIONS

Do not swallow.

Keep out of reach of children.

Read prescribing information fully before using this product. If product is accidentially swallowed in quantities greater than would normally occur with a toothpaste, seek medical help right away.

Sensitive teeth may indicate a serious problem that may need prompt care by a dentist. See your dentist if the problem persists or worsens.

Do not use this product for longer than 4 weeks unless recommended by a dentist or physician.

ADVERSE REACTIONS

To report suspected adverse reactions, contact Dharma Research, Inc. at 1-877-833-3725 or the FDA at 1-800-FDA-1088 or www.fda.gov/medwatch

DESCRIPTION

Ionite H Neutral Fluoride Gel is a flavored, pH neutral 1.1% sodium fluoride, 5% potassium nitrate gel that aids in the prevention of dental decay and hleps to treat sensitive teeth.

ACTIVE INGREDIENTS

Sodium Fluoride, 1.1%; Potassium Nitrate, 5%

INACTIVE INGREDIENTS

Alpha-tocopheryl, carbopol, edetic acid, flavor, glycerin, sodium hydroxide, sodium polymetaphosphate, tricalcium phosphate, water, xylitol

HOW SUPPLIED/STORAGE

4.3 ounces (122 g) in a plastic tube. Store at room temperature 59 – 86°F (15 – 30°C).

Manufactured by Dharma Research, Inc.

www.dharmaresearch.com

5220 N.W. 72 Avenue, Unit 15

Miami, FL 33166

1-877-833-3725

Ionite H

NDC 53045-281-04

Home Care

1.1% Neutral Fluoride Gel

with Xylitol and Vitamin E

Bubble Gum

Rx Only

Made in USA

Gluten Free Dye Free

Re-order#: 56-00141

4.3 oz. (122 g)